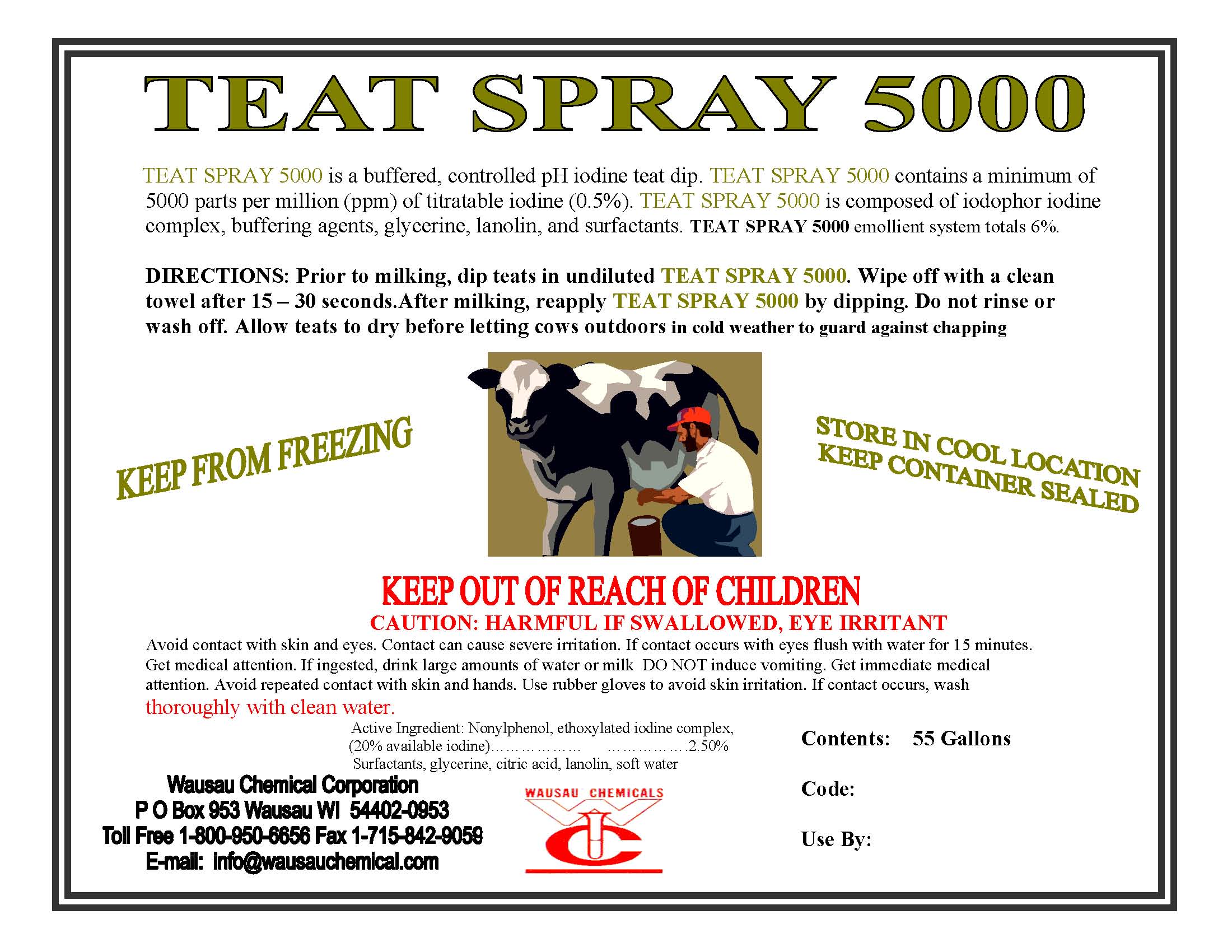 DRUG LABEL: Teat Spray 5000
NDC: 64892-001 | Form: SOLUTION
Manufacturer: Wausau Chemical
Category: animal | Type: OTC ANIMAL DRUG LABEL
Date: 20000914

ACTIVE INGREDIENTS: IODINE 0.5 L/100 L

GENERAL PRECAUTIONS

FOR COMMERCIAL USE ONLY

KEEP OUT OF REACH OF CHILDREN

NOT FOR HUMAN USE

CAUTION

Harmful if swallowed, eye irritant.

FIRST AID:

Avoid contact with skin and eyes. Contact can cause severe irritation. Get medical attention. If ingested, drink large amounts of water or milk. DO NOT induce vomiting. Get immediate attention. Avoid repeated contact with skin and hands. Use rubber gloves to avoid skin irritation. If contact occurs, wash thoroughly with clean water.

EMERGENCY: CHEMTREC 800-424-9300

VETERINARY INDICATIONS

Prior to milking, dip teats in undiluted Teat Spray 5000. Wipe off with a clean towel after 15 to 30 seconds.

After milking apply Teat Spray 5000 by dipping. Do not rinse or wash off. Allow teats to dry before letting

cows outdoors in cold weather to guard against chapping.

PACKAGE LABEL

Teat Spray 5000

Iodine Teat Spray

An aid in Reducing the Spread of Organisms

Which May Cause Mastitis

ACTIVE INGREDIENTS:

Iodine.........................................0.5%

INACTIVE INGREDIENTS............99.5%

Wausau Chemical Corporation

2001 North River Drive

Wausau, WI 54403-0953 U.S.A.